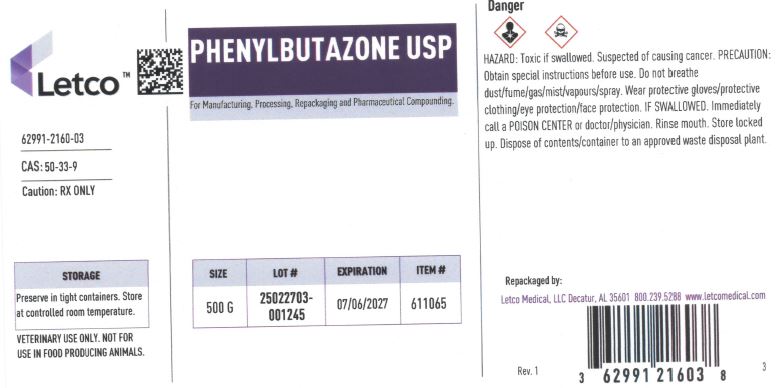 DRUG LABEL: Phenylbutazone
NDC: 62991-2160 | Form: POWDER
Manufacturer: LETCO MEDICAL, LLC
Category: other | Type: BULK INGREDIENT - ANIMAL DRUG
Date: 20250627

ACTIVE INGREDIENTS: PHENYLBUTAZONE 1 g/1 g

Phenylbutazone

PACKAGE LABEL

Phenylbutazone USP 500g